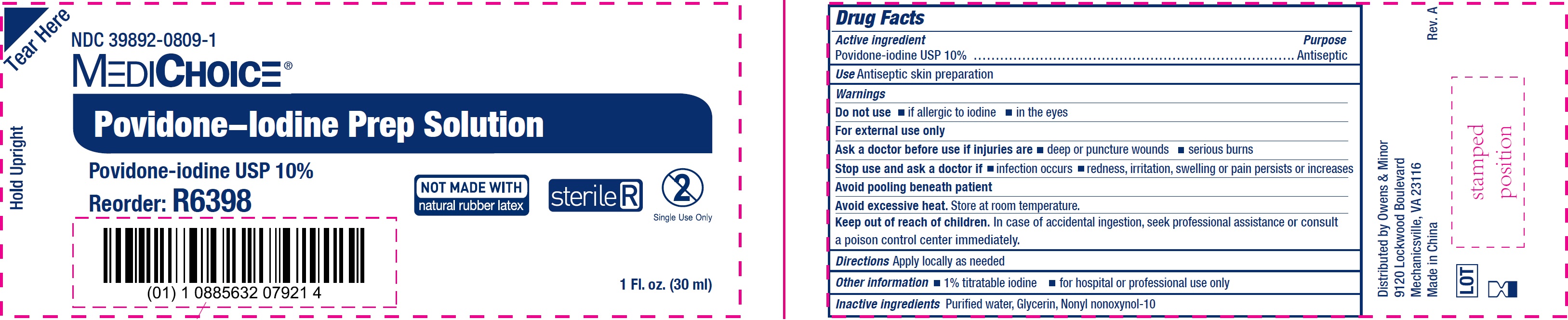 DRUG LABEL: Povidone-Iodine Prep
NDC: 39892-0809 | Form: SOLUTION
Manufacturer: O&M HALYARD, INC.
Category: otc | Type: HUMAN OTC DRUG LABEL
Date: 20251009

ACTIVE INGREDIENTS: POVIDONE-IODINE 100 mg/1 mL
INACTIVE INGREDIENTS: WATER; GLYCERIN

Povidone-Iodine Prep Solution

Active ingredient

Povidone-iodine USP 10%

Purpose

Antiseptic

Use

Antiseptic skin preparation

Warnings

For external use only

Do not use

• if allergic to iodine • in the eyes

Ask a doctor before use

if injuries are • deep or puncture wounds • serious burns

Stop use and ask a doctor if

• infection occurs • redness, irritation, swelling or pain persists or increases

Avoid pooling beneath patient

Avoid excessive heat. Store at room temperature.

Keep out of reach of children.

In case of accidental ingestion, seek professional assistance or consult a poison control center immediately.

Directions

Apply locally as needed

Other information

• 1% titratable iodine • for hospital or professional use only

Inactive ingredients

Purified water, Glycerin, Nonyl nonoxynol-10